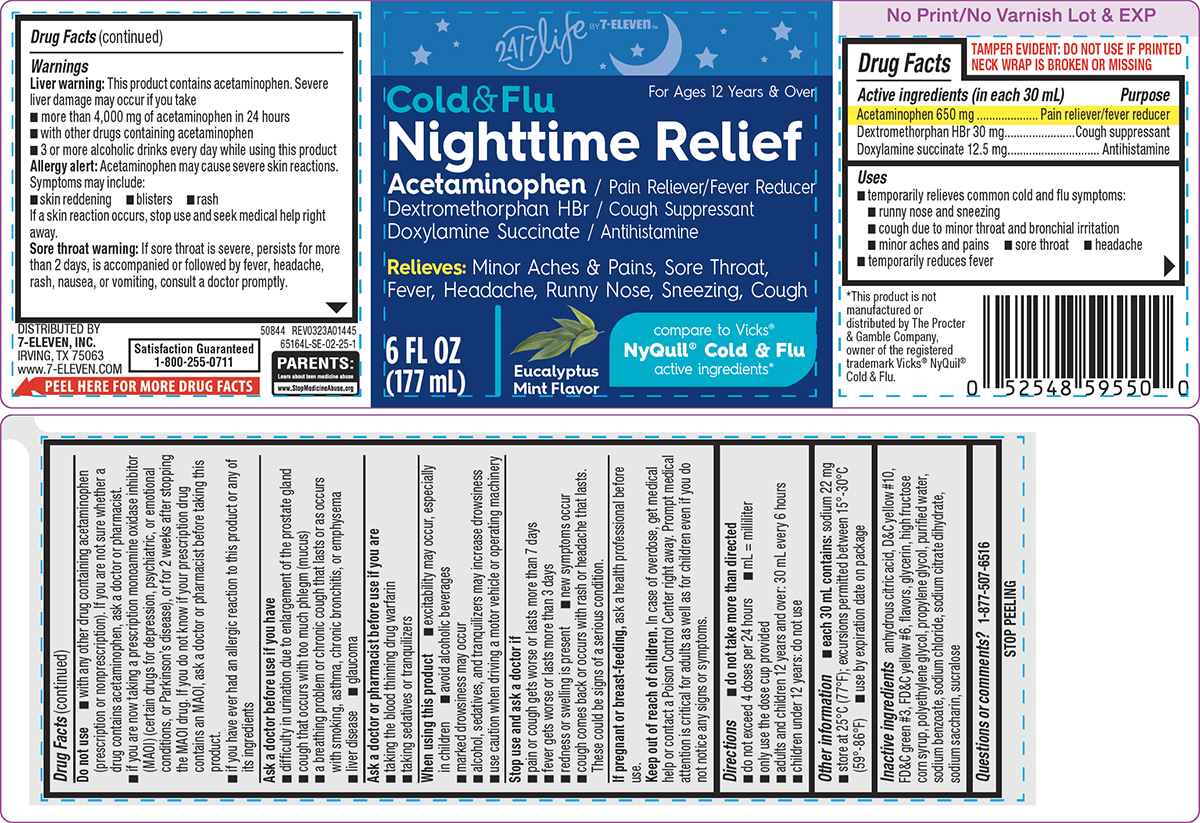 DRUG LABEL: Cold and Flu Nighttime Relief
NDC: 50844-252 | Form: SOLUTION
Manufacturer: L.N.K. International, Inc.
Category: otc | Type: HUMAN OTC DRUG LABEL
Date: 20251219

ACTIVE INGREDIENTS: ACETAMINOPHEN 650 mg/30 mL; DEXTROMETHORPHAN HYDROBROMIDE 30 mg/30 mL; DOXYLAMINE SUCCINATE 12.5 mg/30 mL
INACTIVE INGREDIENTS: ANHYDROUS CITRIC ACID; D&C YELLOW NO. 10; FD&C GREEN NO. 3; FD&C YELLOW NO. 6; GLYCERIN; HIGH FRUCTOSE CORN SYRUP; POLYETHYLENE GLYCOL, UNSPECIFIED; PROPYLENE GLYCOL; WATER; SODIUM BENZOATE; SODIUM CHLORIDE; TRISODIUM CITRATE DIHYDRATE; SACCHARIN SODIUM; SUCRALOSE

Convenience Valet 44-014

Active ingredients (in each 30 mL)

Acetaminophen 650 mg
Dextromethorphan HBr 30 mg
Doxylamine succinate 12.5 mg

Purpose

Pain reliever/fever reducer
Cough suppressant
Antihistamine

Uses

- temporarily relieves common cold and flu symptoms:
  - runny nose and sneezing
  - cough due to minor throat and bronchial irritation
  - minor aches and pains
  - sore throat
  - headache
- temporarily reduces fever

Warnings

Liver warning: This product contains acetaminophen. Severe liver damage may occur if you take

- more than 4,000 mg of acetaminophen in 24 hours
- with other drugs containing acetaminophen
- 3 or more alcoholic drinks every day while using this product

Allergy alert: Acetaminophen may cause severe skin reactions. Symptoms may include:

- skin reddening
- blisters
- rash

If a skin reaction occurs, stop use and seek medical help right away.

Sore throat warning: If sore throat is severe, persists for more than 2 days, is accompanied or followed by fever, headache, rash, nausea, or vomiting, consult a doctor promptly.

Do not use

- with any other drug containing acetaminophen (prescription or nonprescription). If you are not sure whether a drug contains acetaminophen, ask a doctor or pharmacist.
- if you are now taking a prescription monoamine oxidase inhibitor (MAOI) (certain drugs for depression, psychiatric, or emotional conditions, or Parkinson’s disease), or for 2 weeks after stopping the MAOI drug. If you do not know if your prescription drug contains an MAOI, ask a doctor or pharmacist before taking this product.
- if you have ever had an allergic reaction to this product or any of its ingredients

Ask a doctor before use if you have

- difficulty in urination due to enlargement of the prostate gland
- cough that occurs with too much phlegm (mucus)
- a breathing problem or chronic cough that lasts or as occurs with smoking, asthma, chronic bronchitis, or emphysema
- liver disease
- glaucoma

Ask a doctor or pharmacist before use if you are

- taking the blood thinning drug warfarin
- taking sedatives or tranquilizers

When using this product

- excitability may occur, especially in children
- avoid alcoholic beverages
- marked drowsiness may occur
- alcohol, sedatives, and tranquilizers may increase drowsiness
- use caution when driving a motor vehicle or operating machinery

Stop use and ask a doctor if

- pain or cough gets worse or lasts more than 7 days
- fever gets worse or lasts more than 3 days
- redness or swelling is present
- new symptoms occur
- cough comes back or occurs with rash or headache that lasts. These could be signs of a serious condition.

If pregnant or breast-feeding,

ask a health professional before use.

Keep out of reach of children.

In case of overdose, get medical help or contact a Poison Control Center right away. Prompt medical attention is critical for adults as well as for children even if you do not notice any signs or symptoms.

Directions

- do not take more than directed
- do not exceed 4 doses per 24 hours
- mL = milliliter
- only use the dose cup provided
- adults and children 12 years and over: 30 mL every 6 hours
- children under 12 years: do not use

Other information

- each 30 mL contains: sodium 22 mg
- store at 25°C (77°F); excursions permitted between 15°-30°C (59°-86°F)
- use by expiration date on package

Inactive ingredients

anhydrous citric acid, D&C yellow #10, FD&C green #3, FD&C yellow #6, flavors, glycerin, high fructose corn syrup, polyethylene glycol, propylene glycol, purified water, sodium benzoate, sodium chloride, sodium citrate dihydrate, sodium saccharin, sucralose

Questions or comments?

1-877-507-6516

Principal display panel

24/7 life
BY 7-ELEVEN™

For Ages 12 Years & Over

Cold & Flu
Nighttime Relief

Acetaminophen / Pain Reliever/Fever Reducer
Dextromethorphan HBr / Cough Suppressant
Doxylamine Succinate / Antihistamine

Relieves: Minor Aches & Pains, Sore Throat,
Fever, Headache, Runny Nose, Sneezing, Cough

compare to Vicks®
NyQuil® Cold & Flu
active ingredients*

6 FL OZ
(177 mL)

Eucalyptus
Mint Flavor

TAMPER EVIDENT: DO NOT USE IF PRINTED
NECK WRAP IS BROKEN OR MISSING

PARENTS:
Learn about teen medicine abuse
www.StopMedicineAbuse.org

*This product is not
manufactured or
distributed by The Procter
& Gamble Company,
owner of the registered
trademark Vicks® NyQuil®
Cold & Flu.

50844 REV0323A01445

DISTRIBUTED BY
7-ELEVEN, INC.
IRVING, TX 75063
www.7-ELEVEN.COM

Satisfaction Guaranteed
1-800-255-0711

Convenience Valet 44-014